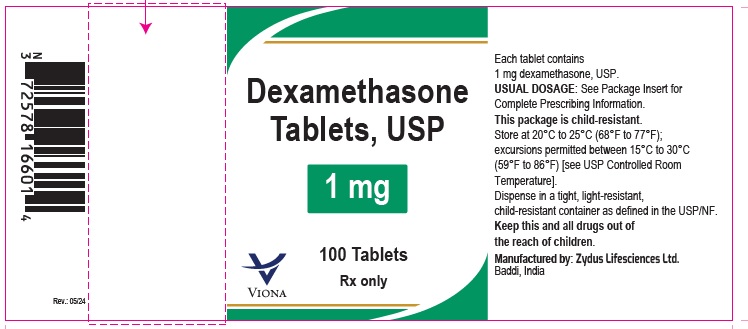 DRUG LABEL: Dexamethasone
NDC: 70771-1706 | Form: TABLET
Manufacturer: Zydus Lifesciences Limited
Category: prescription | Type: HUMAN PRESCRIPTION DRUG LABEL
Date: 20240513

ACTIVE INGREDIENTS: DEXAMETHASONE 1 mg/1 1
INACTIVE INGREDIENTS: FERRIC OXIDE YELLOW; LACTOSE MONOHYDRATE; MAGNESIUM STEARATE; STARCH, CORN; SUCROSE

Dexamethasone Tablets, USP

PACKAGE LABEL.PRINCIPAL DISPLAY PANEL

NDC 70771-1706-1

Dexamethasone Tablets, USP 1 mg

100 Tablets

Rx only